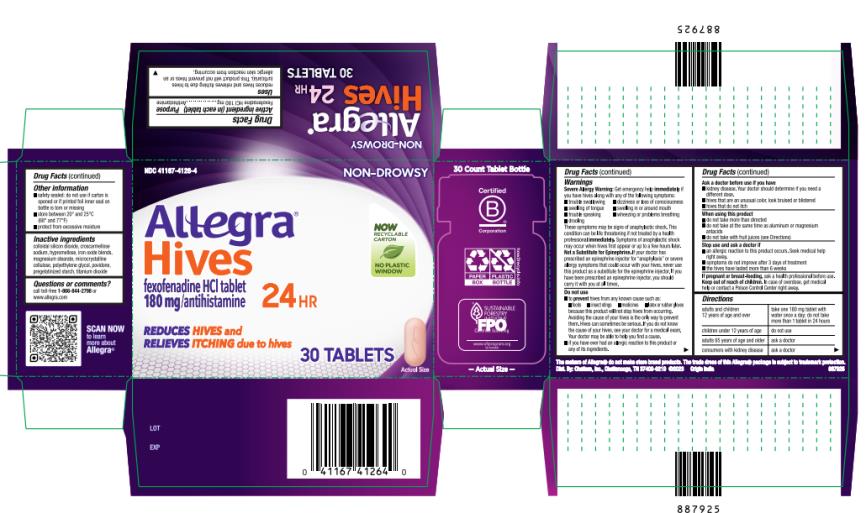 DRUG LABEL: Allegra Hives 24hr
NDC: 41167-4126 | Form: TABLET, FILM COATED
Manufacturer: Chattem, Inc.
Category: otc | Type: HUMAN OTC DRUG LABEL
Date: 20240601

ACTIVE INGREDIENTS: FEXOFENADINE HYDROCHLORIDE 180 mg/1 1
INACTIVE INGREDIENTS: SILICON DIOXIDE; CROSCARMELLOSE SODIUM; HYPROMELLOSE, UNSPECIFIED; BROWN IRON OXIDE; MAGNESIUM STEARATE; MICROCRYSTALLINE CELLULOSE; POLYETHYLENE GLYCOL, UNSPECIFIED; POVIDONE; STARCH, CORN; TITANIUM DIOXIDE

Allegra Hives 24HR

Allegra Hives 24HR tablet 180 mg

Drug Facts

Active ingredient (in each tablet)

Fexofenadine HCl 180 mg

Purpose

Antihistamine

Uses

reduces hives and relieves itching due to hives (urticaria). This product will not prevent hives or an allergic skin reaction from occurring.

Warnings

Severe Allergy Warning: Get emergency help immediately if you have hives along with any of the following symptoms:

■ trouble swallowing ■ dizziness or loss of consciousness ■ swelling of tongue

■ swelling in or around mouth ■ trouble speaking ■ wheezing or problems breathing ■ drooling

These symptoms may be signs of anaphylactic shock. This condition can be life threatening if not treated by a health professional immediately. Symptoms of anaphylactic shock may occur when hives first appear or up to a few hours later.

Not a Substitute for Epinephrine. If your doctor has prescribed an epinephrine injector for “anaphylaxis” or severe allergy symptoms that could occur with your hives, never use this product as a substitute for the epinephrine injector. If you have been prescribed an epinephrine injector, you should carry it with you at all times.

Do not use

■ to prevent hives from any known cause such as:

■ foods ■ insect stings ■ medicines ■ latex or rubber gloves because this product will not stop hives from occurring. Avoiding the cause of your hives is the only way to prevent them. Hives can sometimes be serious. If you do not know the cause of your hives, see your doctor for a medical exam. Your doctor may be able to help you find a cause.

■ if you have ever had an allergic reaction to this product or any of its ingredients.

Ask a doctor before use if you have

■ kidney disease. Your doctor should determine if you need a different dose.

■ hives that are an unusual color, look bruised or blistered

■ hives that do not itch

When using this product

■ do not take more than directed

■ do not take at the same time as aluminum or magnesium antacids

■ do not take with fruit juices (see Directions)

Stop use and ask a doctor if

■ an allergic reaction to this product occurs. Seek medical help right away.

■ symptoms do not improve after 3 days of treatment

■ the hives have lasted more than 6 weeks

If pregnant or breast-feeding,

ask a health professional before use.

Keep out of reach of children.

In case of overdose, get medical help or contact a Poison Control Center right away.

Directions

adults and children 12 years of age and over | take one 180 mg tablet with water once a day; do not take more than 1 tablet in 24 hours
children under 12 years of age | do not use
adults 65 years of age and older | ask a doctor
consumers with kidney disease | ask a doctor

Other information

■(if blister) safety sealed: do not use if carton is opened or if individual blister units are torn or opened

■(on the carton if bottle) safety sealed: do not use if carton is opened or if printed foil inner seal on bottle is torn or missing

■(if bottle) safety sealed: do not use if carton was opened or if printed foil inner seal on bottle is torn or missing

■ store between 20° and 25°C (68° and 77°F)

■ protect from excessive moisture

Inactive ingredients

colloidal silicon dioxide, croscarmellose sodium, hypromellose, iron oxide blends, magnesium stearate, microcrystalline cellulose, polyethylene glycol, povidone, pregelatinized starch, titanium dioxide

Questions or comments?

call toll-free 1-800-633-1610

PRINCIPAL DISPLAY PANEL

Allegra
Hives
fexofenadine HCI tablet
180 mg/antihistamine
24 HR
30 TABLETS